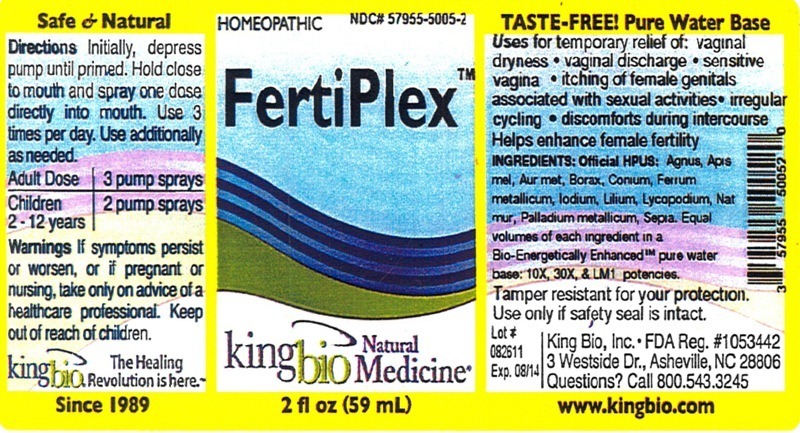 DRUG LABEL: FertiPlex
NDC: 57955-5005 | Form: LIQUID
Manufacturer: King Bio Inc.
Category: homeopathic | Type: HUMAN OTC DRUG LABEL
Date: 20120410

ACTIVE INGREDIENTS: CHASTE TREE 10 [hp_X]/59 mL; APIS MELLIFERA 10 [hp_X]/59 mL; GOLD 10 [hp_X]/59 mL; SODIUM BORATE 10 [hp_X]/59 mL; CONIUM MACULATUM FLOWERING TOP 10 [hp_X]/59 mL; IRON 10 [hp_X]/59 mL; IODINE 10 [hp_X]/59 mL; LILIUM LANCIFOLIUM WHOLE FLOWERING 10 [hp_X]/59 mL; LYCOPODIUM CLAVATUM SPORE 10 [hp_X]/59 mL; SODIUM CHLORIDE 10 [hp_X]/59 mL; PALLADIUM 10 [hp_X]/59 mL; SEPIA OFFICINALIS JUICE 10 [hp_X]/59 mL
INACTIVE INGREDIENTS: WATER

FertiPlex

Active Ingredients

Official HPUS: Agnus castus, Apis Mellifica, Aurum Metallicum, Borax, Conium maculatum, Ferrum metallicum, Iodium, Lilium tigrinum, Lycopodium clavatum, Natrum muriaticum, Palladium Metallicum and Sepia.

Reference image fertiplex.jpg

Inactive Ingredients

Equal volumes of each ingredient in a Bio-Energetically Enhanced pure water base: 10X, 30X, and LM1 potencies.

Reference image fertiplex.jpg

Purpose

Uses for temporary relief of:

- vaginal dryness
- vaginal discharge
- sensitive vagina
- itching of female genitals associated with sexual activities
- irregular cycling
- discomforts during intercourse

Helps enhance female fertility.
Reference image fertiplex.jpg

Dosage and Administration

Directions Initially, depress pump until primed. Hold close to mouth and spray one dose directly into mouth. Use 3 times per day. Use additionally as needed.

Adult Dose 3 pump sprays

Children 2-12 years 2 pump sprays

Reference image fertiplex.jpg

Warnings

If symptoms persist or worsen, or if pregnant or nursing, take only on advice of a healthcare professional. Keep out of reach of children.

Other Tamper resistant for your protection. Use only if safety seal is intact.

Reference image fertiplex.jpg

Keep out of reach of children.

Reference image fertiplex.jpg

Indications and Usage

Uses for temporary relief of: vaginal dryness, vaginal discharge, sensitive vagina, itching of female genitals associated with sexual activities, irregular cycling, discomforts during intercourse.

Helps enhance female fertility.

Reference image fertiplex.jpg

PACKAGE LABEL

King Bio Inc.

3 Westside Drive

Asheville, NC 28806

Questions? Call 800.543.3245

www.kingbio.com

Reference image fertiplex.jpg